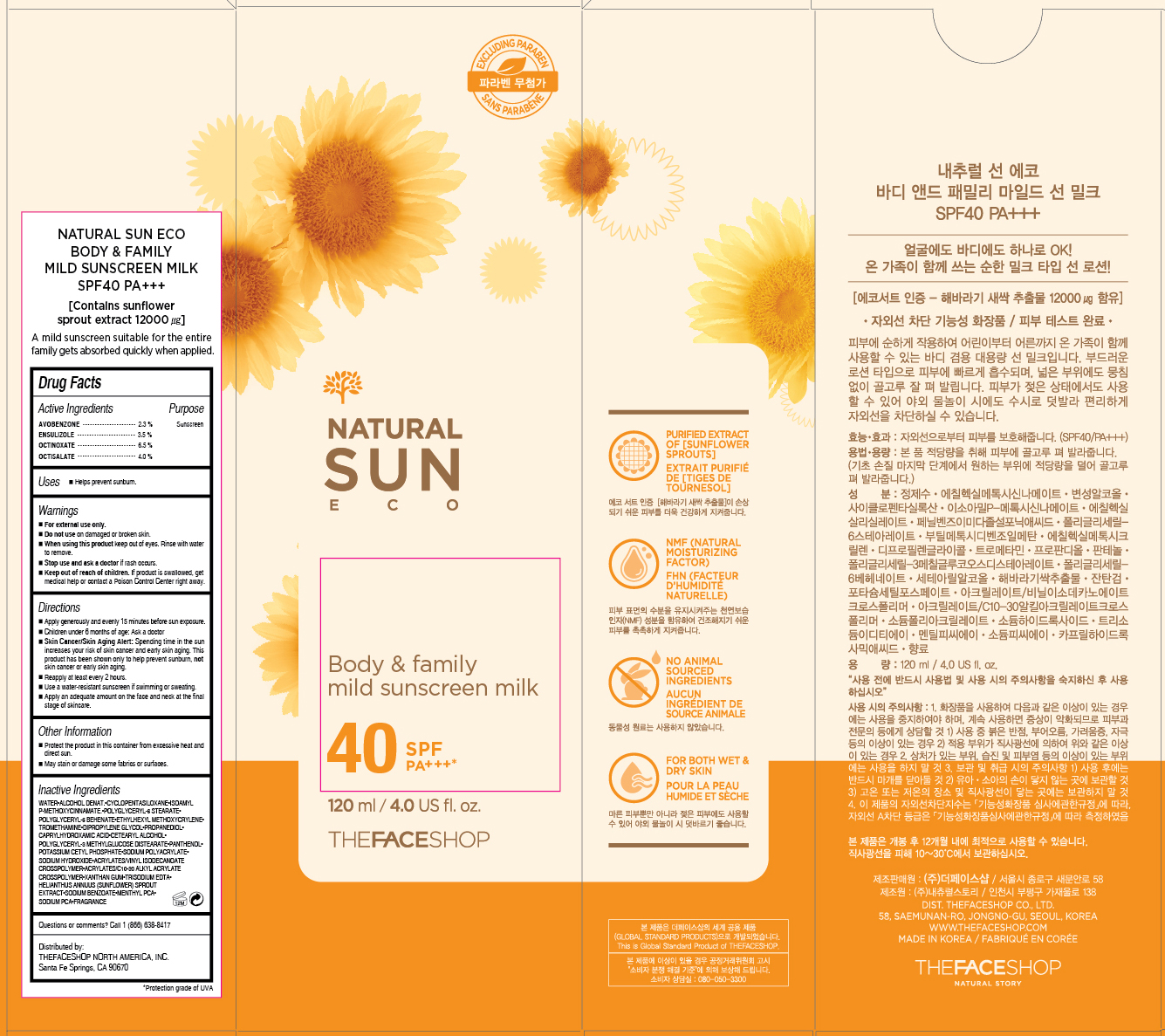 DRUG LABEL: NATURAL SUN ECO
NDC: 51523-174 | Form: LOTION
Manufacturer: THEFACESHOP CO., LTD.
Category: otc | Type: HUMAN OTC DRUG LABEL
Date: 20150929

ACTIVE INGREDIENTS: AVOBENZONE 2.76 g/120 mL; ENSULIZOLE 4.2 g/120 mL; OCTISALATE 4.8 g/120 mL; OCTINOXATE 7.8 g/120 mL
INACTIVE INGREDIENTS: WATER

NATURAL SUN ECO BODY & FAMILY MILD SUNSCREEN MILK 40 SPF PA+++ 31500174

Active Ingredient

Avobenzone 2.3%
Ensulizole 3.5%
Octinoxate 6.5%
Octisalate 4.0%

Purpose

Sunscreen
Sunscreen
Sunscreen
Sunscreen

Uses:

Helps prevent sunburn.

Warnings

For external use only.

Do not use on damaged or broken skin

When using this product keep out of eyes. Rinse with water to remove.

Stop use and ask a doctor if rash occurs.

Keep out of reach of children. If product is swallowed, get medical help or contact a Poison Control Center right away.

Directions

Apply generously and evenly 15 minutes before sun exposure.
Children under 6 months of age: Ask a doctor.
Skin Cancer/Skin Aging Alert: Spending time in the sun increases your risk of skin cancer and early skin aging. This product has been shown only to help prevent sunburn, not skin cancer or early skin aging.
Reapply at least every 2 hours.
Use a water-resistant sunscreen if swimming or sweating.

Apply an adequate amount on the face and neck at the final stage of skincare.

OTHER SAFETY INFORMATION

Protect the product in this container from excessive heat and direct sun.

May stain or damage some fabrics or surfaces.

Inactive Ingredients

WATER, ALCOHOL DENAT., CYCLOPENTASILOXANE, ISOAMYL P-METHOXYCINNAMATE, POLYGLYCERYL-6 STEARATE, POLYGLYCERYL-6 BEHENATE, ETHYLHEXYL METHOXYCRYLENE, TROMETHAMINE, DIPROPYLENE GLYCOL, PROPANEDIOL, CAPRYLHYDROXAMIC ACID, CETEARYL ALCOHOL, POLYGLYCERYL-3 METHYLGLUCOSE DISTEARATE, PANTHENOL, POTASSIUM CETYL PHOSPHATE, SODIUM POLYACRYLATE, SODIUM HYDROXIDE, ACRYLATES/VINYL ISODECANOATE CROSSPOLYMER, ACRYLATES/C10-30 ALKYL ACRYLATE CROSSPOLYMER, XANTHAN GUM, TRISODIUM EDTA, HELIANTHUS ANNUUS (SUNFLOWER) SPROUT EXTRACT, SODIUM BENZOATE, MENTHYL PCA, SODIUM PCA, FRAGRANCE

Questions or comments? Call 1-866-638-8417

Distributed by:

THEFACESHOP NORTH AMERICA, INC.

Santa Fe Springs, CA 90670

PACKAGE LABEL

NATURAL SUN ECO

BODY & FAMILY MILD SUNSCREEN MILK

SPF 40+ PA+++

Contains sunflower sprout extract 12000 µg

A mild sunscreen suitable for the entire family gets absorbed quickly when applied.